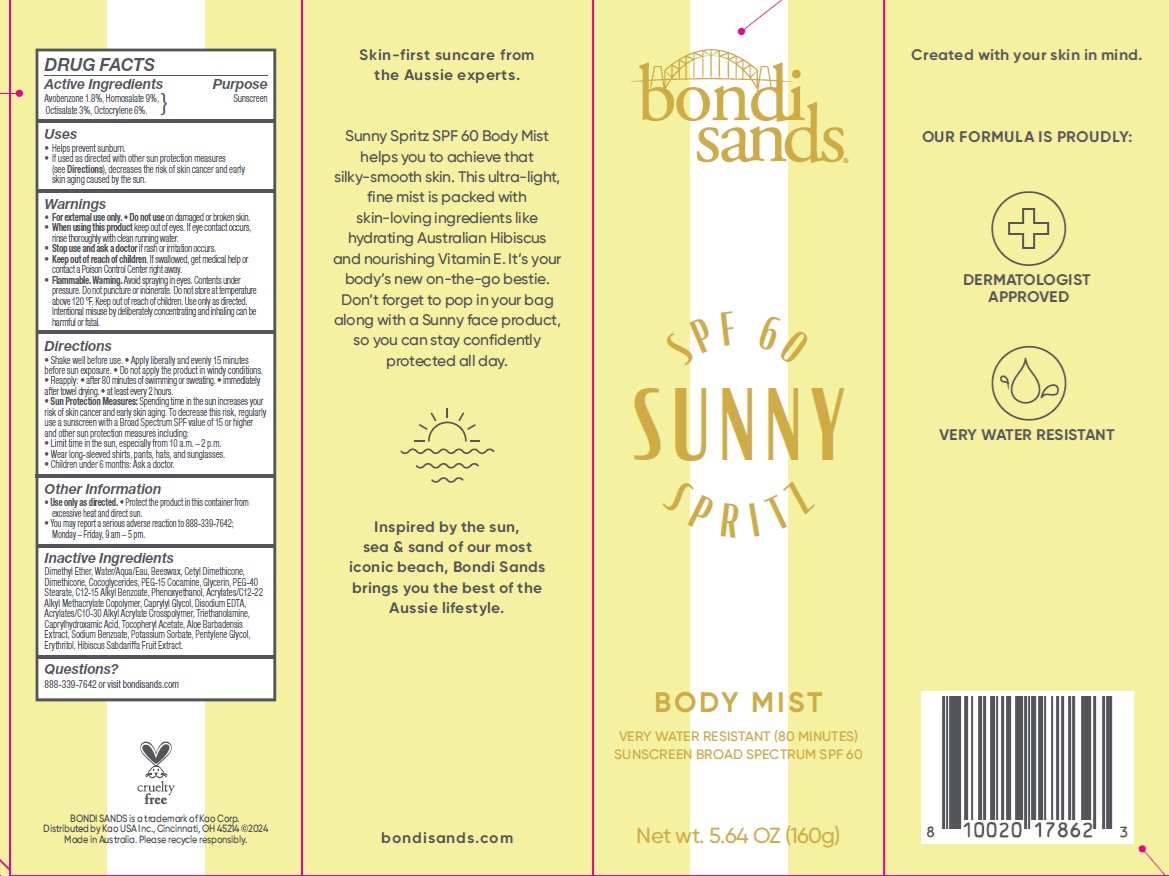 DRUG LABEL: Bondi Sands SPF 60 Sunny Spritz Body Mist
NDC: 79950-017 | Form: AEROSOL, SPRAY
Manufacturer: BONDI SANDS (USA) INC.
Category: otc | Type: HUMAN OTC DRUG LABEL
Date: 20250106

ACTIVE INGREDIENTS: OCTISALATE 30 mg/1 g; OCTOCRYLENE 60 mg/1 g; AVOBENZONE 18 mg/1 g; HOMOSALATE 90 mg/1 g
INACTIVE INGREDIENTS: PENTYLENE GLYCOL; POTASSIUM SORBATE; .ALPHA.-TOCOPHEROL ACETATE; EDETATE DISODIUM; ALOE VERA WHOLE; SODIUM BENZOATE; BEESWAX; CETYL DIMETHICONE 45; DIMETHICONE; PEG-15 COCAMINE; PEG-40 STEARATE; WATER; PHENOXYETHANOL; C12-15 ALKYL BENZOATE; GLYCERIN; DIMETHYL ETHER; CAPRYLYL GLYCOL; TROLAMINE; ERYTHRITOL; COCOGLYCERIDES; ACRYLATES/C10-30 ALKYL ACRYLATE CROSSPOLYMER (60000 MPA.S); CAPRYLHYDROXAMIC ACID

Bondi Sands SPF 60 Sunny Spritz Body Mist

Active Ingredients

Avobenzone 1.8%

Homosalate 9%

Octisalate 3%

Octocrylene 6%

Purpose

Sunscreen

Uses

- Helps prevent sunburn.
- If used as directed with other sun protection measures (see Directions), decreases the risk of skin cancer and early skin aging caused by the sun.

Warnings

- For external use only.

Do not use

on damaged or broken skin.

When using this product

keep out of eyes. If eye contact occurs, rinse thoroughly with clean running water.

Stop use and ask a doctor

if rash or irritation occurs.

Keep out of reach of children.

If swallowed, get medical help or contact a Poison Control Center right away.

Flammable. Warning.

Avoid spraying in eyes. Contents under pressure. Do not puncture or incinerate. Do not store at temperature above 120 °F. Keep out of reach of children. Use only as directed. Intentional misuse by deliberately concentrating and inhaling can be harmful or fatal.

Directions

- Shake well before use.
- Apply liberally and evenly 15 minutes before sun exposure.
- Do not apply the product in windy conditions.
- Reapply:
- after 80 minutes of swimming or sweating.
- immediately after towel drying.
- at least every 2 hours.
- Sun Protection Measures: Spending time in the sun increases your risk of skin cancer and early skin aging. To decrease this risk, regularly use a sunscreen with a Broad Spectrum SPF value of 15 or higher and other sun protection measures including:
- Limit time in the sun, especially from 10 a.m. – 2 p.m.
- Wear long-sleeved shirts, pants, hats, and sunglasses.
- Children under 6 months: Ask a doctor.

Other Information

- Use only as directed.
- Protect the product in this container from excessive heat and direct sun.
- You may report a serious adverse reaction to 888-339-7642; Monday – Friday, 9 am – 5 pm.

Inactive Ingredients

Dimethyl Ether, Water/Aqua/Eau, Beeswax, Cetyl Dimethicone, Dimethicone, Cocoglycerides, PEG-15 Cocamine, Glycerin, PEG-40 Stearate, C12-15 Alkyl Benzoate, Phenoxyethanol, Acrylates/C12-22 Alkyl Methacrylate Copolymer, Caprylyl Glycol, Disodium EDTA, Acrylates/C10-30 Alkyl Acrylate Crosspolymer, Triethanolamine, Caprylhydroxamic Acid, Tocopheryl Acetate, Aloe Barbadensis Extract, Sodium Benzoate, Potassium Sorbate, Pentylene Glycol, Erythritol, Hibiscus Sabdariffa Fruit Extract.

Questions?

888-339-7642 or visit bondisands.com